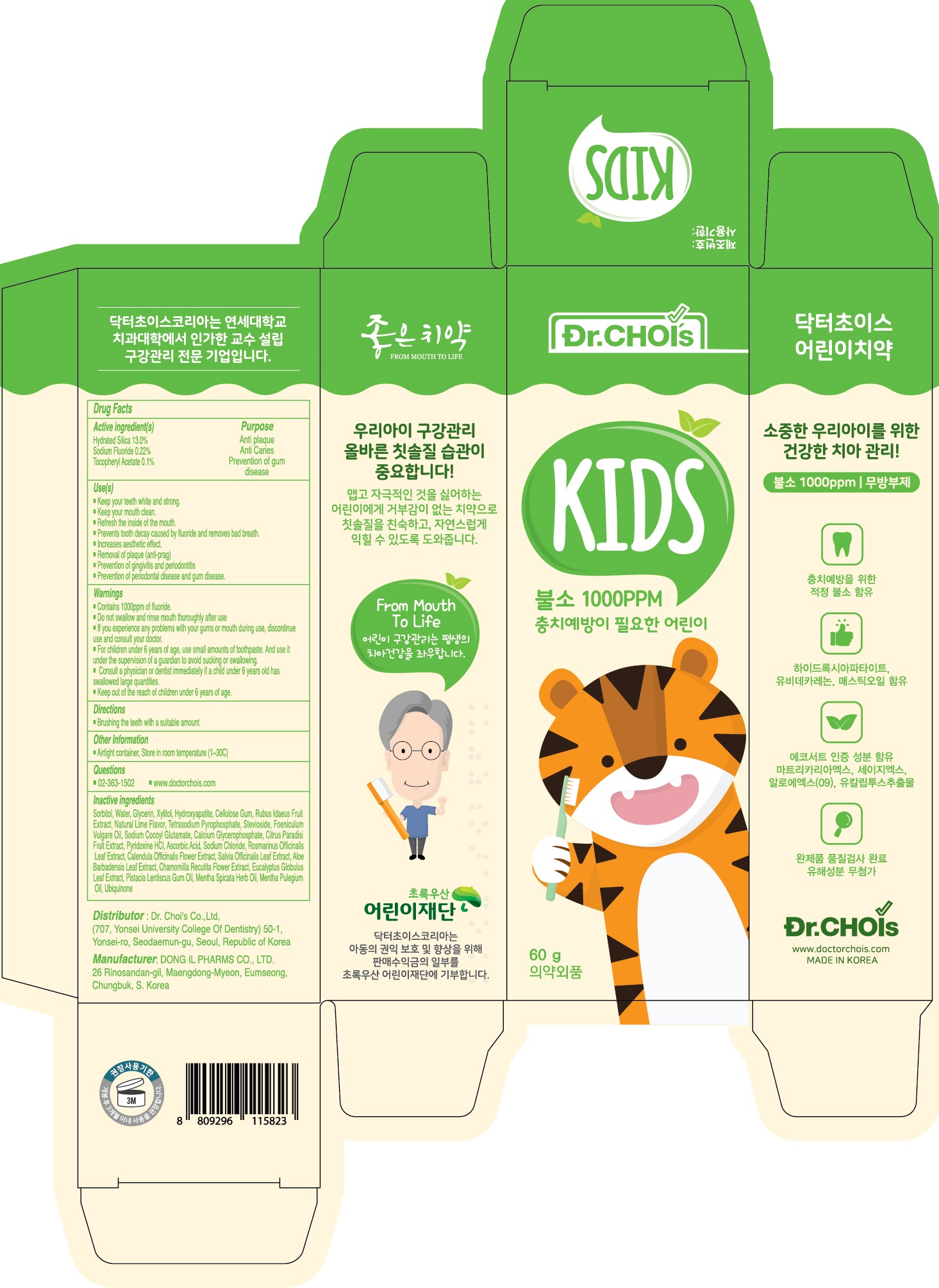 DRUG LABEL: Dr.Chois KF Toothpaste
NDC: 73666-0600 | Form: PASTE, DENTIFRICE
Manufacturer: Doctor Choi`s Korea Co., LTD.
Category: otc | Type: HUMAN OTC DRUG LABEL
Date: 20240416

ACTIVE INGREDIENTS: SILICON DIOXIDE 13.0 g/100 g; Sodium Fluoride 0.22 g/100 g; .ALPHA.-TOCOPHEROL ACETATE 0.1 g/100 g
INACTIVE INGREDIENTS: Sorbitol; Water; Glycerin

ACTIVE INGREDIENTS

Hydrated Silica 13.0%
Sodium Fluoride 0.22%
Tocopheryl Acetate 0.1%

PURPOSE

Anti plaque
Anti Caries
Prevention of gum disease

Uses

■ Keep your teeth white and strong.
■ Keep your mouth clean.
■ Refresh the inside of the mouth.
■ Prevents tooth decay caused by fluoride and removes bad breath.
■ Increases aesthetic effect.
■ Removal of plaque (anti-prag)
■ Prevention of gingivitis and periodontitis
■ Prevention of periodontal disease and gum disease.

WARNINGS

■ Contains 1000ppm of fluoride.
■ Do not swallow and rinse mouth thoroughly after use
■ If you experience any problems with your gums or mouth during use,
discontinue use and consult your doctor.
■ For children under 6 years of age, use small amounts of toothpaste. And use it
under the supervision of a guardian to avoid sucking or swallowing.
■ Consult a physician or dentist immediately if a child under 6 years old has
swallowed large quantities.
■ Keep out of the reach of children under 6 years of age.

KEEP OUT OF REACH OF CHILDREN

■ Keep out of the reach of children under 6 years of age.

Directions

■ Brushing the teeth with a suitable amount

Other Information

■ Airtight container, Store in room temperature (1~30C)

Questions

■ 02-363-1502
■ www.doctorchois.com

INACTIVE INGREDIENTS

Sorbitol, Water, Glycerin, Xylitol, Hydroxyapatite, Cellulose Gum, Rubus Idaeus Fruit Extract, Natural Lime Flavor, Tetrasodium Pyrophosphate, Stevioside, Foeniculum Vulgare Oil, Sodium Cocoyl Glutamate, Calcium Glycerophosphate, Citrus Paradisi Fruit Extract, Pyridoxine HCl, Ascorbic Acid, Sodium Chloride, Rosmarinus Officinalis Leaf Extract, Calendula Officinalis Flower Extract, Salvia Officinalis Leaf Extract, Aloe Barbadensis Leaf Extract, Chamomilla Recutita Flower Extract, Eucalyptus Globulus Leaf Extract, Pistacia Lentiscus Gum Oil, Mentha Spicata Herb Oil, Mentha Pulegium Oil, Ubiquinone